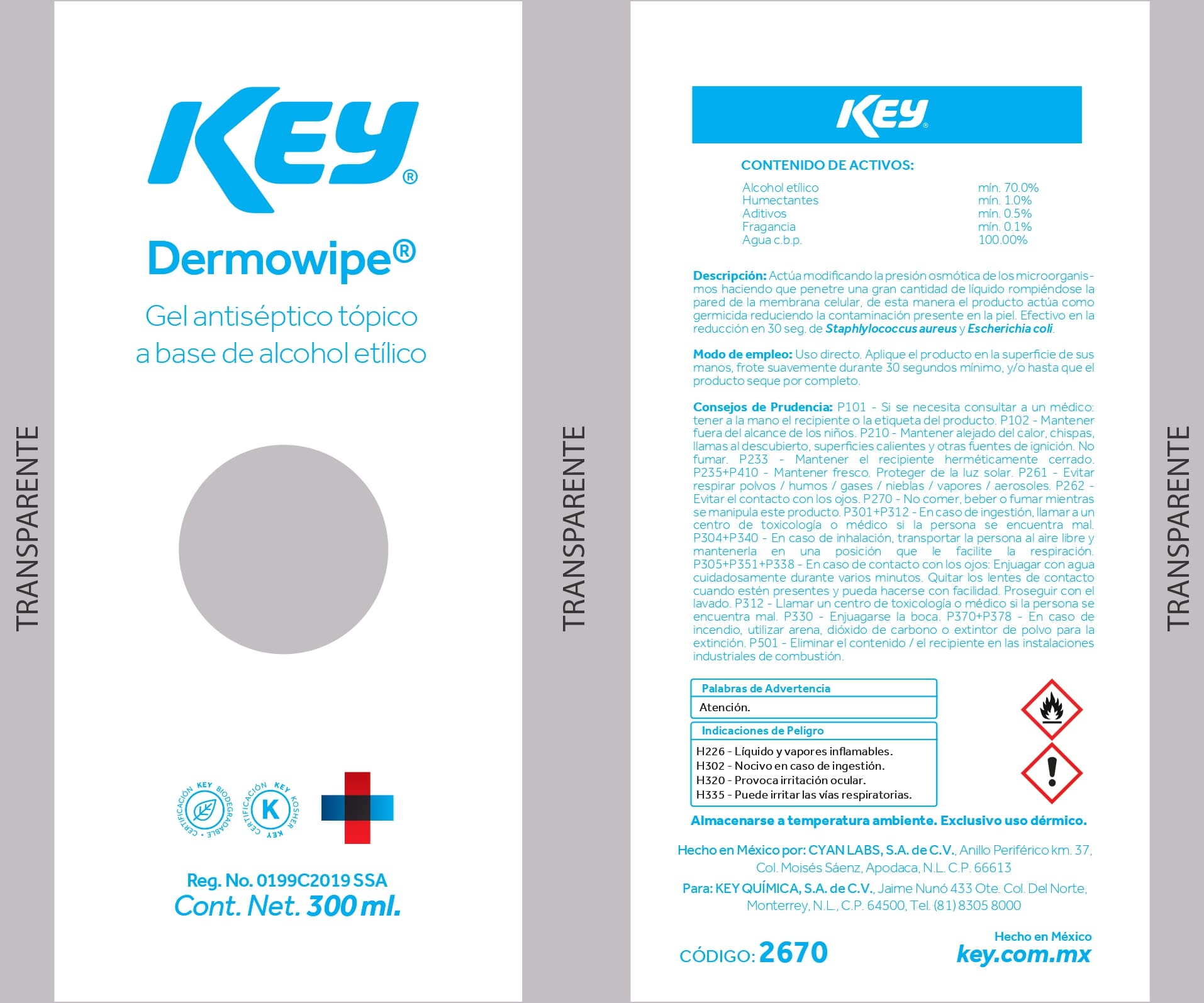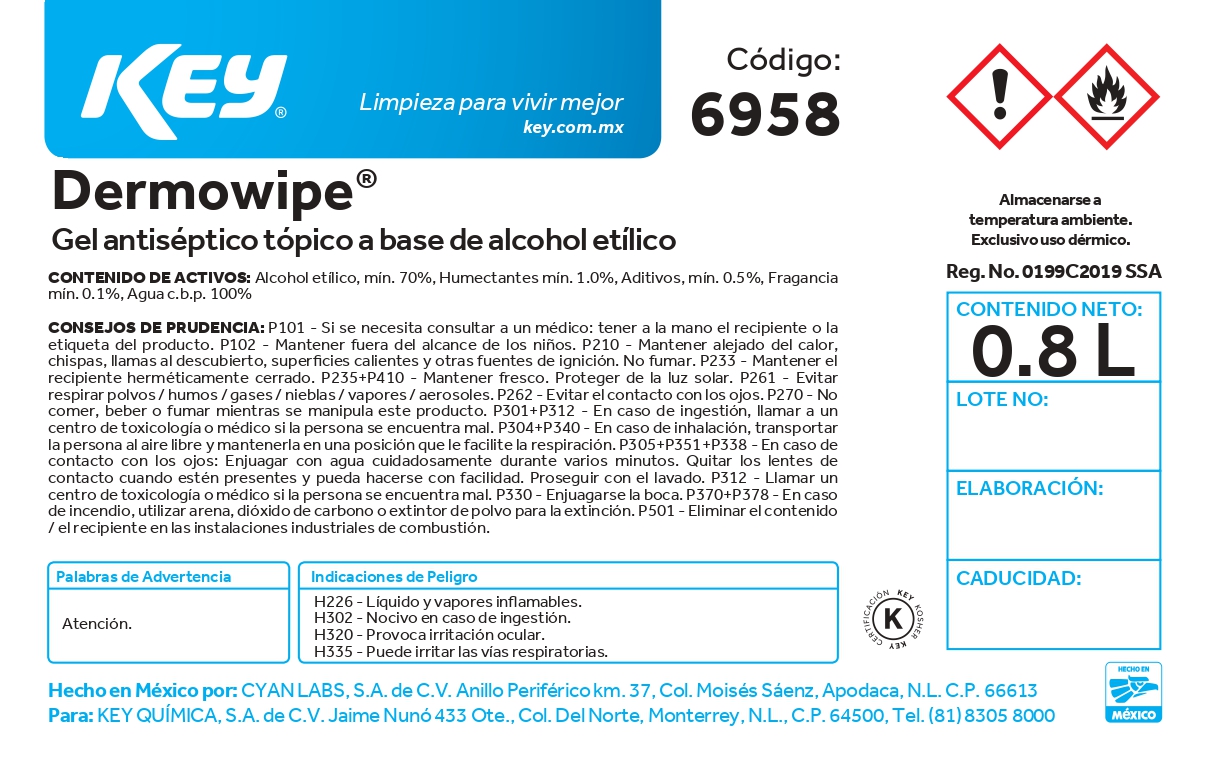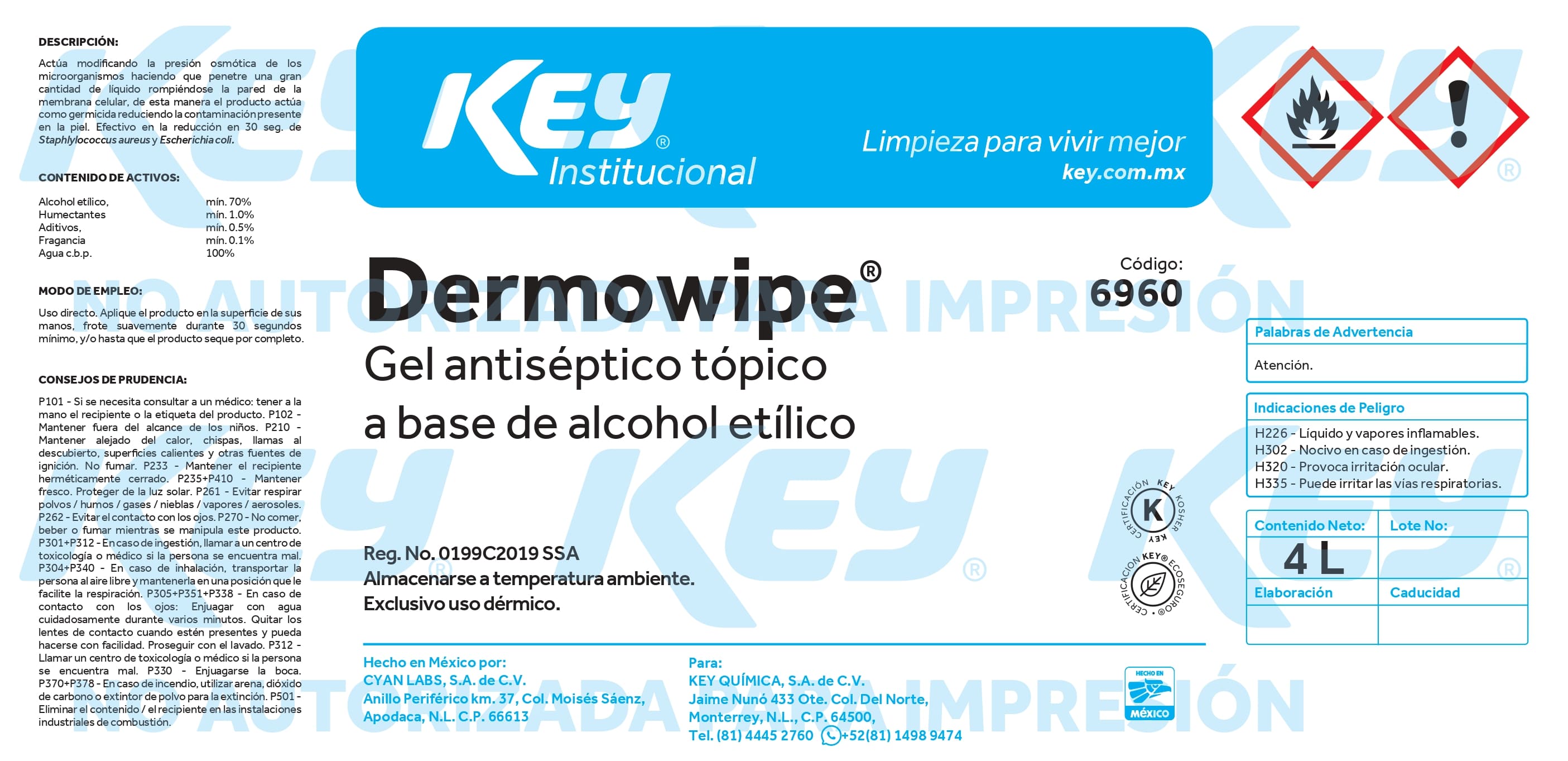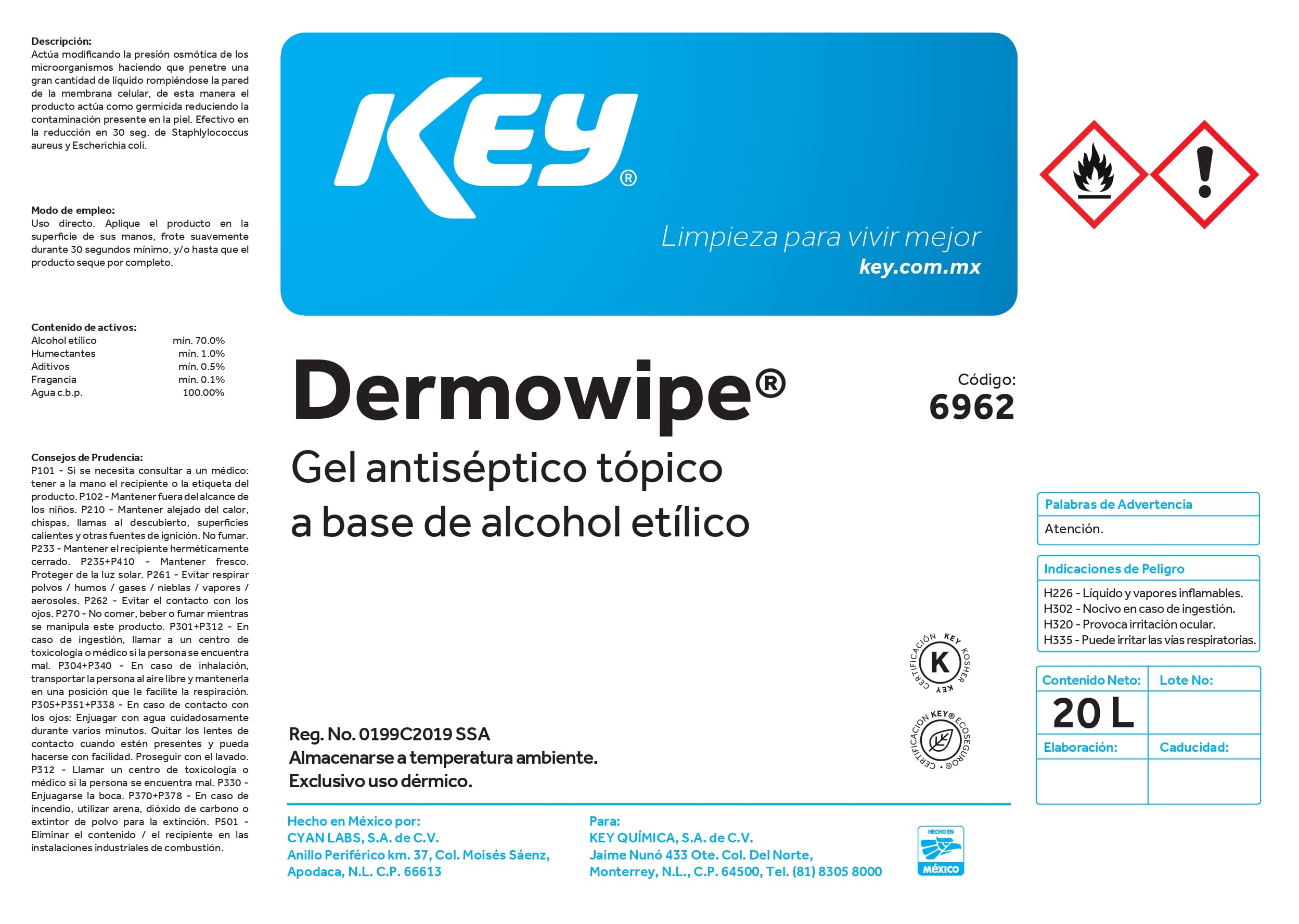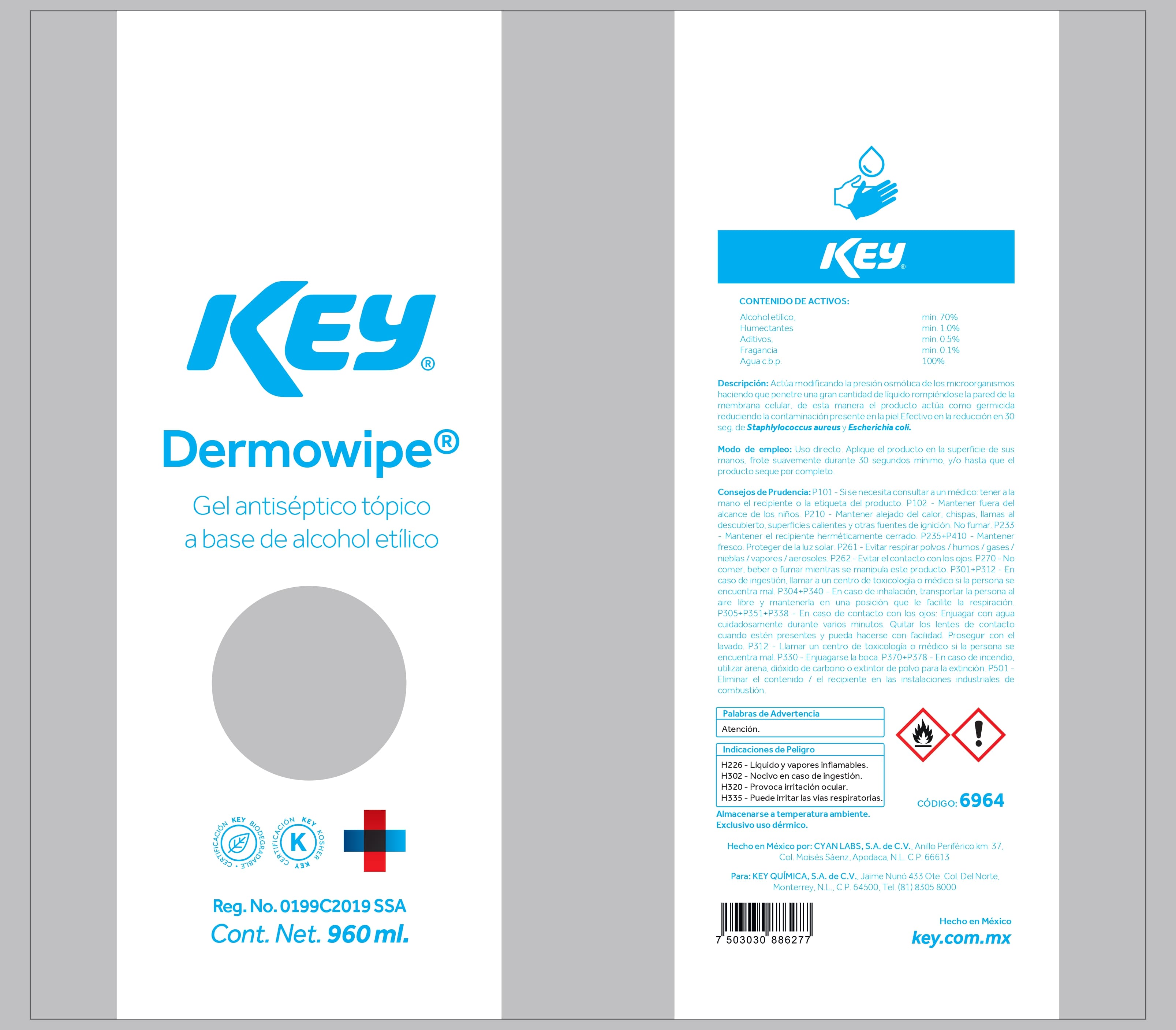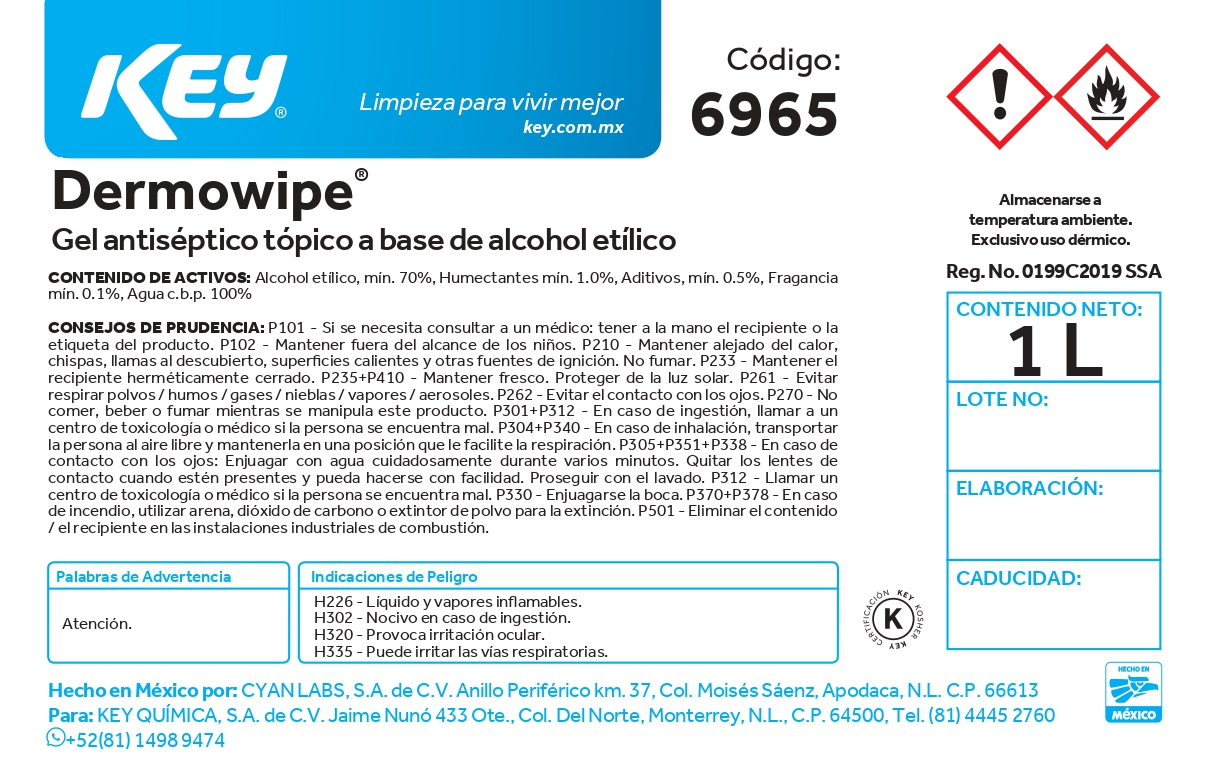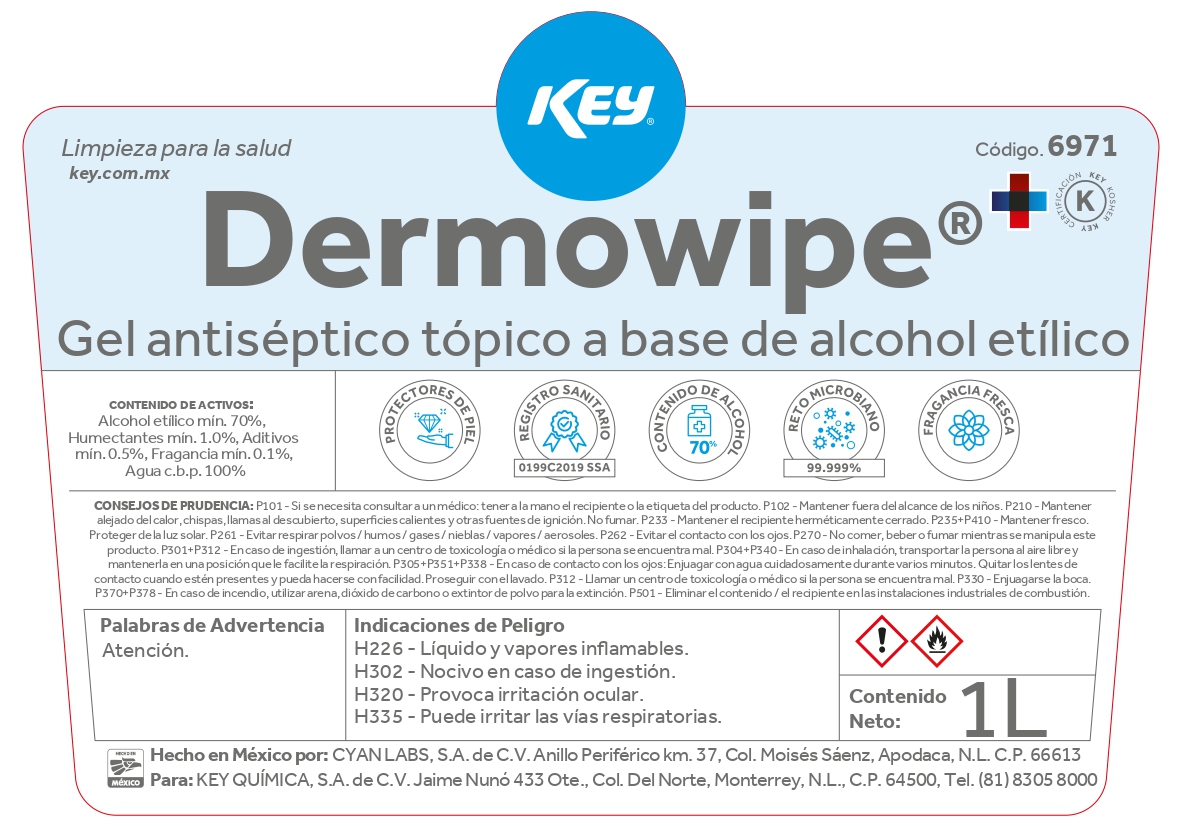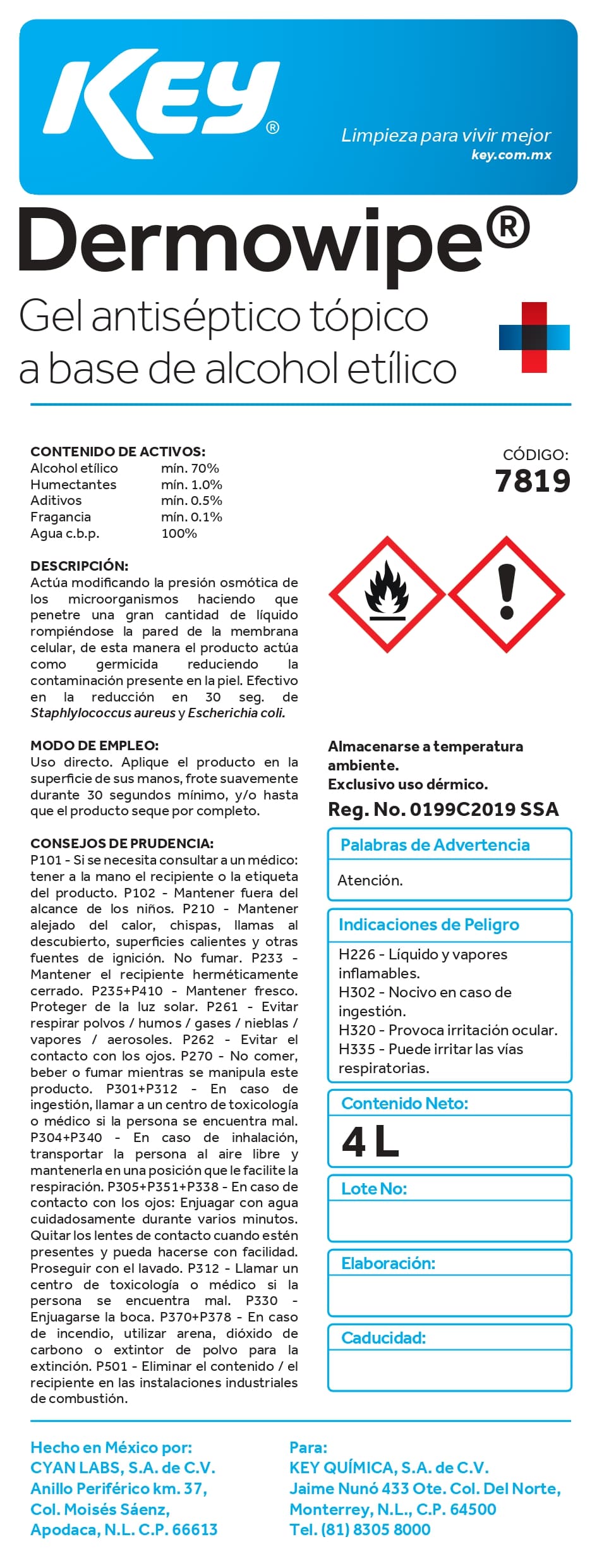 DRUG LABEL: Gel Antiseptico Dermowipe
NDC: 58345-103 | Form: GEL
Manufacturer: Key Química S.A. de C.V.
Category: otc | Type: HUMAN OTC DRUG LABEL
Date: 20250107

ACTIVE INGREDIENTS: ALCOHOL 70 mL/70 mL
INACTIVE INGREDIENTS: ALPHA-TOCOPHEROL; TRIETHANOLAMINE LAURYL SULFATE; ACRYLATES/C10-30 ALKYL ACRYLATE CROSSPOLYMER (60000 MPA.S); GLYCERIN; GLYCERETH-7 TRIACETATE; WATER

58345-103

Contenido de activos

Alcohol etílico mín. 70.0 %

Humectantes mín. 1.0 %

Aditivos mín. 0.5 %

Fragancia mín. 0.1 %

Agua c.b.p. 100.00 %

Descripción

Actúa modificando la presión osmótica de los microorganis- mos haciendo que penetre una gran cantidad de líquido rompiéndose la pared de la membrana celular, de esta manera el producto actúa como germicida reduciendo la contaminación presente en la piel. Efectivo en la reducción en 30 seg. de Staphlylococcus aureus y Escherichia coli.

Modo de empleo

Uso directo. Aplique el producto en la superficie de sus manos, frote suavemente durante 30 segundos mínimo, y/o hasta que el producto seque por completo.

Consejos de prudencia

P101 - Si se necesita consultar a un médico: tener a la mano el recipiente o la etiqueta del producto. P102 - Mantener fuera del alcance de los niños. P210 - Mantener alejado del calor, chispas, llamas al descubierto, superficies calientes y otras fuentes de ignición. No fumar. P233 - Mantener el recipiente herméticamente cerrado. P235+P410 - Mantener fresco. Proteger de la luz solar. P261 - Evitar respirar polvos / humos / gases / nieblas / vapores / aerosoles. P262 - Evitar el contacto con los ojos. P270 - No comer, beber o fumar mientras se manipula este producto. P301+P312 - En caso de ingestión, llamar a un centro de toxicología o médico si la persona se encuentra mal. P304+P340 - En caso de inhalación, transportar la persona al aire libre y mantenerla en una posición que le facilite la respiración. P305+P351+P338 - En caso de contacto con los ojos: Enjuagar con agua cuidadosamente durante varios minutos. Quitar los lentes de contacto cuando estén presentes y pueda hacerse con facilidad. Proseguir con el lavado. P312 - Llamar un centro de toxicología o médico si la persona se encuentra mal. P330 - Enjuagarse la boca. P370+P378 - En caso de incendio, utilizar arena, dióxido de carbono o extintor de polvo para la extinción. P501 - Eliminar el contenido / el recipiente en las instalaciones industriales de combustión.

Palabras de advertencia

Atención

Indicaciones de peligro

H226 - Líquido y vapores inflamables.

H302 - Nocivo en caso de ingestión.

H320 - Provoca irritación ocular.
H335 - Puede irritar las vías respiratorias.

Active ingredient

Acohol 70 % v/v

Purpose

Antiseptic

Do not use this product in or near the eyes.

Stop use if irritation or redness develop. If conditions persist for more than 72 hours, consult a doctor.

Keep out of reach of children. If swallowed, seek inmediate medical attention or call a poison control center.

Inactive ingredients

Water (aqua), Glycerin, Carbopol, Triethanolamine, Fragance, Glycereth-7 triacetate and Tocopherol.